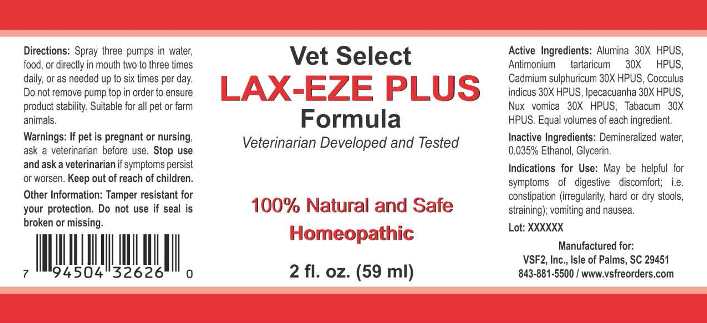 DRUG LABEL: Lax-Eze Plus
NDC: 86100-0001 | Form: LIQUID
Manufacturer: Vsf2, Inc.
Category: homeopathic | Type: OTC ANIMAL DRUG LABEL
Date: 20251110

ACTIVE INGREDIENTS: ALUMINUM OXIDE 30 [hp_X]/1 mL; ANTIMONY POTASSIUM TARTRATE 30 [hp_X]/1 mL; CADMIUM SULFATE 30 [hp_X]/1 mL; ANAMIRTA COCCULUS SEED 30 [hp_X]/1 mL; IPECAC 30 [hp_X]/1 mL; STRYCHNOS NUX-VOMICA SEED 30 [hp_X]/1 mL; TOBACCO LEAF 30 [hp_X]/1 mL
INACTIVE INGREDIENTS: WATER; ALCOHOL; GLYCERIN

Drug Facts:

ACTIVE INGREDIENTS:

Alumina 30X HPUS, Antimonium Tartaricum 30X HPUS, Cadmium Sulphuricum 30X HPUS, Cocculus Indicus 30X HPUS, Ipecacuanha 30X HPUS, Tabacum 30X HPUS.

Equal volumes of each ingredient.

INDICATIONS FOR USE:

May be helpful for symptoms of digestive discomfort; i.e. constipation (irregularity, hard or dry stools, straining); vomiting and nausea.

WARNINGS:

If pet is pregnant or nursing, ask a veterinarian before use.

Stop use and ask a veterinarian if symptoms persist or worsen.

Keep out of reach of children.

Other Information: Tamper resistant for your protection. Do not use if seal is broken or missing.

KEEP OUT OF THE REACH OF CHILDREN:

Keep out of reach of children.

DIRECTIONS:

Spray three pumps in water, food or directly in mouth two to three times daily, or as needed up to six times per day. Do not remove pump top in order to ensure product stability. Suitable for all pet or farm animals.

INDICATIONS FOR USE:

May be helpful for symptoms of digestive discomfort; i.e. constipation (irregularity, hard or dry stools, straining); vomiting and nausea.

INACTIVE INGREDIENTS:

Demineralized water, 0.035% Ethanol, Glycerin.

QUESTIONS:

Manufactured for:

VSF2, Inc., Isle of Palms, SC 29451

843-881-5500 / www.vsfreorders.com

PACKAGE LABEL DISPLAY:

Vet Select

LAX-EZE PLUS

Formula

Veterinarian Developed and Tested

100% Natural and Safe

Homeopathic

2 fl. oz. (59 ml)